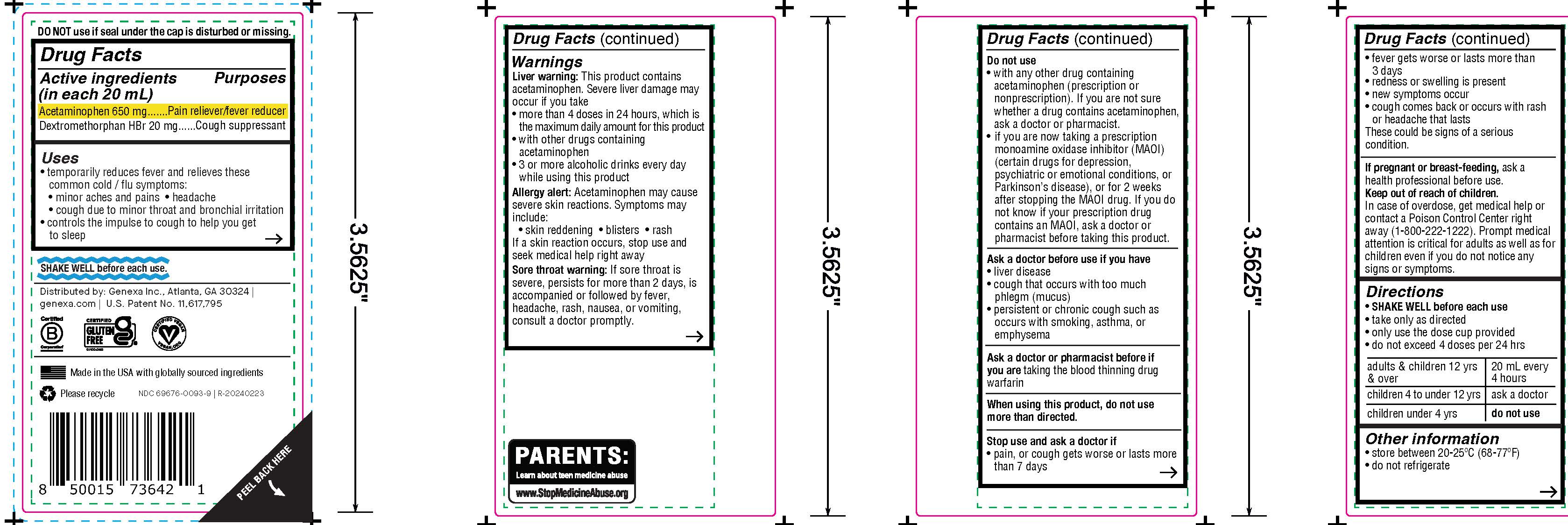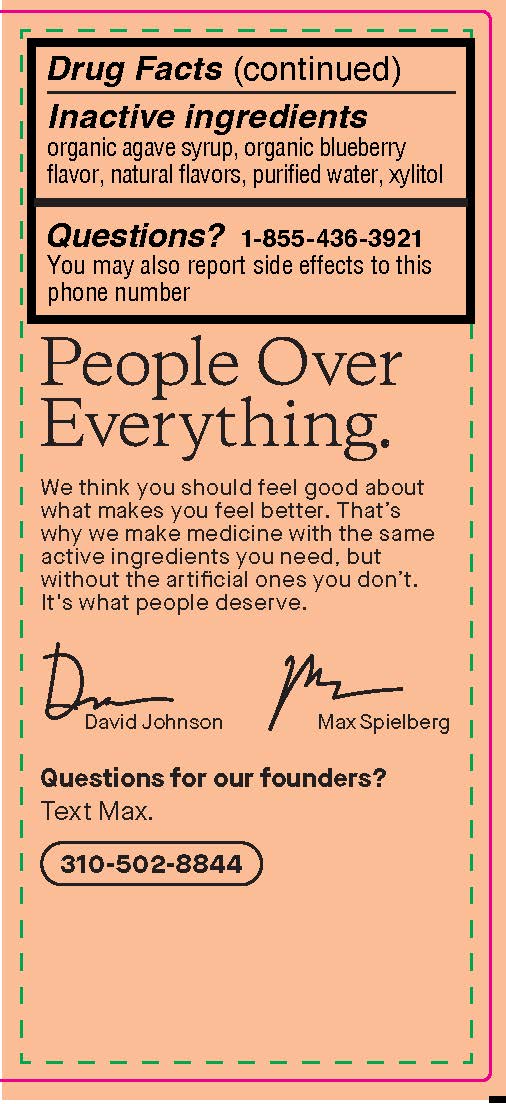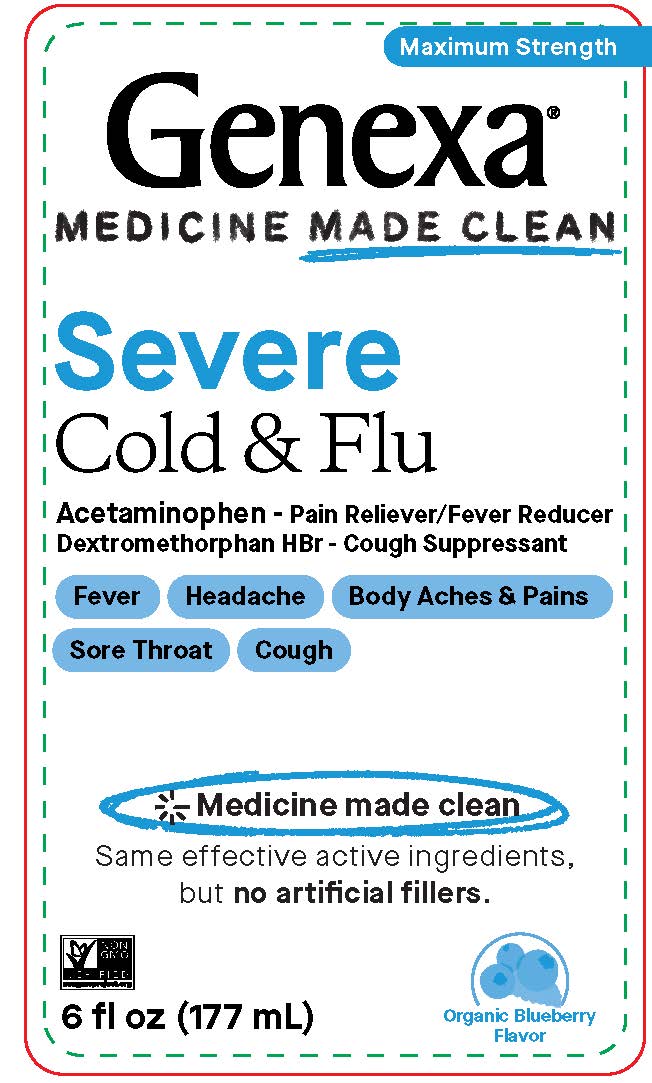 DRUG LABEL: Daytime Severe Cold and Flu
NDC: 69676-0093 | Form: SUSPENSION
Manufacturer: Genexa Inc.
Category: otc | Type: HUMAN OTC DRUG LABEL
Date: 20250207

ACTIVE INGREDIENTS: DEXTROMETHORPHAN HYDROBROMIDE 20 mg/20 mL; ACETAMINOPHEN 650 mg/20 mL
INACTIVE INGREDIENTS: AGAVE TEQUILANA JUICE; XYLITOL; BLUEBERRY; WATER

Daytime Severe Cold and Flu

DO NOT use if seal under the cap is disturbed or missing.

Drug Facts

Active ingredients

(in each 20 mL)

Acetaminophen 650 mg

Dextromethorphan HBr 20 mg

Purposes

Pain reliever/fever reducer

Cough suppressant

Uses

- temporarily reduces fever and relieves these common cold/flu symptoms:
- minor aches and pains
- headache
- cough due to minor throat and bronchial irritation

- controls the impulse to cough to help you get to sleep

SHAKE WELL before each use.

Distributed by: Genexa Inc., Atlanta, GA 30324 |

genexa.com | U.S. Patent No. 11,617,795

Made in the USA with globally sourced ingredients

NDC 69676-0093-9

Warnings

Liver warning: This product contains acetaminophen. Severe liver damage may occur if you take

- more than 4 doses in 24 hours, which is the maximum daily amount for this product
- with other drugs containing acetaminophen
- 3 or more alcoholic drinks every day while using this product

Allergy alert: Acetaminophen may cause severe skin reactions. Symptoms may include:

- skin reddening
- blisters
- rash

If a skin reaction occurs, stop use and seek medical help right away

Sore throat warning: If sore throat is severe, persists for more than 2 days, is accompanied or followed by fever, headache, rash, nausea, or vomiting, consult a doctor promptly.

Do not use

- with any other drug containing acetaminophen (prescription or nonprescription). If you are not sure whether a drug contains acetaminophen, ask a doctor or pharmacist
- if you are now taking a prescription monoamine oxidase inhibitor (MAOI) (certain drugs for depression, psychiatric or emotional conditions, or Parkinson's disease), or for 2 weeks after stopping the MAOI drug. If you do not know if your prescription drug contains an MAOI, ask a doctor or pharmacist before taking this product.

Ask a doctor before use if you have

- liver disease
- cough that occurs with too much phlegm (mucus)
- persistent or chronic cough such as occurs with smoking, asthma, or emphysema

Ask a doctor or pharmacist before use if you are taking the blood thinning drug warfarin

When using this product, do not use more than directed.

Stop use and ask a doctor if

- pain, or cough gets worse or lasts more than 7 days
- fever gets worse or lasts more than 3 days
- redness or swelling is present
- new symptoms occur
- cough comes back or occurs with rash or headache that lasts

These could be signs of a serious condition.

PREGNANCY OR BREAST FEEDING

If pregnant or breast-feeding, ask a health professional before use.

Keep out of reach of children.

OVERDOSAGE

In case of overdose, get medical help or contact a Poison Control Center right away (1-800-222-1222). Prompt medical attention is critical for adults as well as for children even if you do not notice any signs or symptoms.

Directions

- SHAKE WELL before each use
- take only as directed
- only use the dose cup provided
- do not exceed 4 doses per 24 hrs

adults & children 12 yrs & over | 20 mL every 4 hours
children 4 to under 12 yrs | ask a doctor
children under 4 yrs | do not use

Other information

- store between 20-25°C (68-77°F)
- do not refrigerate

Inactive ingredients

organic agave syrup, organic blueberry flavor, natural flavors, purified water, xylitol

Questions? 1-855-436-3921

You may also report side effects to this phone number

PACKAGE LABEL

Maximum Strength

Genexa®

MEDICINE MADE CLEAN

Severe Cold & Flu

Acetaminophen - Pain Reliever/Fever Reducer

Dextromethorphan HBr - Cough Suppressant

Fever

Headache

Body Aches & Pains

Sore Throat

Cough

Medicine made clean

Same effective active ingredients, but no artificial fillers.

6 fl oz (177 mL)

Organic Blueberry Flavor